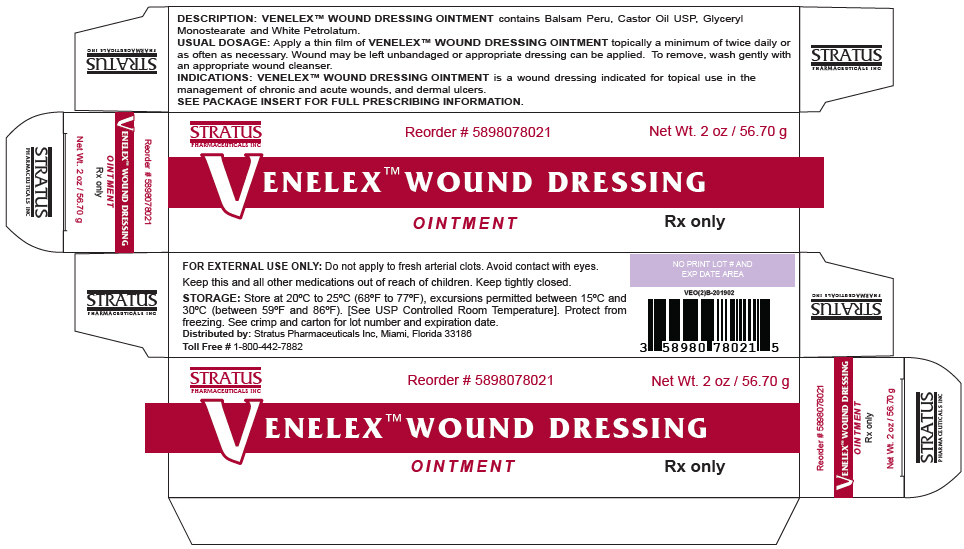 DRUG LABEL: VENELEX
NDC: 58980-780
Manufacturer: STRATUS PHARMACEUTICALS INC
Category: other | Type: MEDICAL DEVICE
Date: 20210401
INACTIVE INGREDIENTS: CASTOR OIL; BALSAM PERU; GLYCERYL MONOSTEARATE; PETROLATUM

VENELEX™ OINTMENT

WOUND DRESSING

Rx Only

DESCRIPTION

VENELEX™ OINTMENT contains Balsam Peru, Castor Oil USP, Glyceryl Monostearate and White Petrolatum.

ACTION

VENELEX™ OINTMENT helps to deodorize and protectively cover pressure wounds (ulcers). VENELEX™ OINTMENT provides a moist wound environment. The moisturizing properties of VENELEX™ OINTMENT may also help in the prevention of cracking around the edges of sores.

INDICATIONS

VENELEX™ OINTMENT is a wound dressing for topical use in the management of chronic and acute wounds, and dermal ulcers including: pressure ulcers (Stage I-IV), venous stasis ulcers, diabetic ulcers, first and second degree burns, surgical wounds, traumatic wounds, superficial wounds, ulcers resulting from arterial insufficiency and grafted wound/donor sites.

CONTRAINDICATIONS

VENELEX™ OINTMENT is contraindicated in persons who have shown hypersensitivity to Balsam Peru, Petrolatum or any of the other ingredients used in this ointment.

USES

VENELEX™ OINTMENT is easy to apply and quickly reduces odors frequently accompanying a decubitus ulcer. The wound may be left open or appropriate dressing applied. Please note that wounds generally heal poorly in the presence of hemoglobin or zinc deficiency.

WARNING

FOR EXTERNAL USE ONLY. Do not apply to fresh arterial clots. Avoid contact with eyes. Keep this and all other medications out of reach of children. Keep tightly closed. Use only as directed by a physician. When applied to a sensitive area, a temporary stinging may occur.

USUAL DOSAGE

Apply a thin film of VENELEX™ OINTMENT topically a minimum of twice daily or as often as necessary. Wound may be left unbandaged or appropriate dressing can be applied. To remove, wash gently with an appropriate wound cleanser.

HOW SUPPLIED

VENELEX™ OINTMENT is supplied as follows:

SIZE | NDC NUMBER
30 GRAM TUBE | 58980-780-11
60 GRAM TUBE | 58980-780-21
5 GRAM PACKETTE × 60 | 58980-780-50

STORAGE

Store at 20°C to 25°C (68°F to 77°F), excursions permitted between 15°C and 30°C (between 59°F and 86°F). Brief exposure to temperatures up to 40°C (104°F) may be tolerated provided the mean kinetic temperature does not exceed 25°C (77°F); however, such exposure should be minimized. [See USP Controlled Room Temperature]. Protect from freezing. See crimp for lot number and expiration date.

Distributed:
Stratus Pharmaceuticals Inc.
Miami, Florida 33186

©2006 Stratus Pharmaceuticals Inc.
Rev. VEOIN2017-0701

PRINCIPAL DISPLAY PANEL - 56.70 g Tube Box

STRATUS
PHARMACEUTICALS INC

Reorder # 5898078021

Net Wt. 2 oz / 56.70 g

VENELEX™ WOUND DRESSING

OINTMENT

Rx only